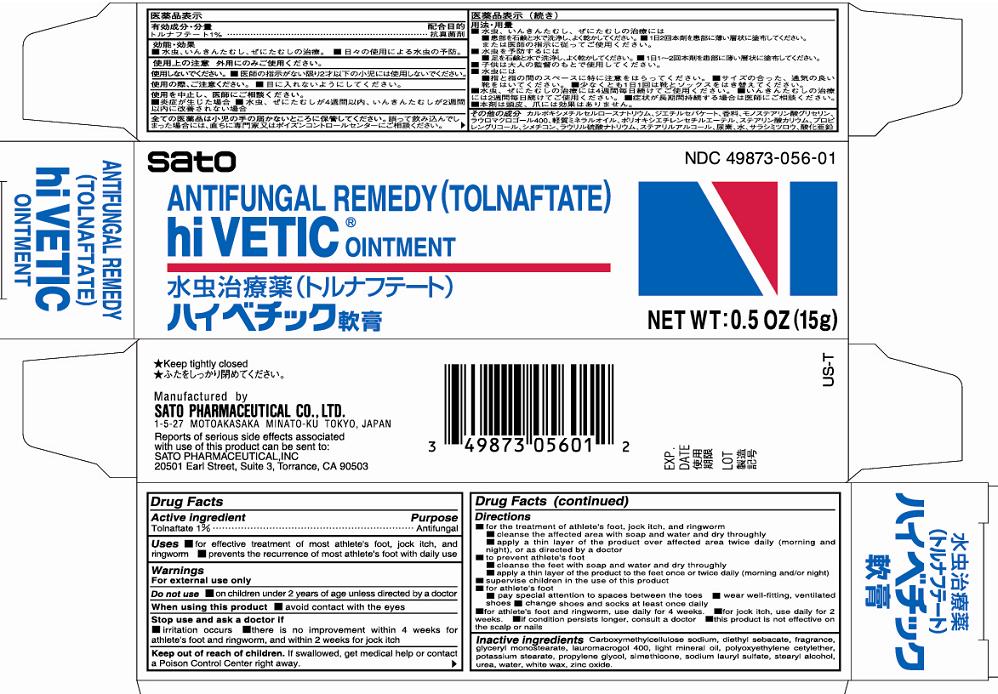 DRUG LABEL: Hi Vetic
NDC: 49873-056 | Form: OINTMENT
Manufacturer: Sato Pharmaceutical Co., Ltd.
Category: otc | Type: HUMAN OTC DRUG LABEL
Date: 20231206

ACTIVE INGREDIENTS: TOLNAFTATE 1 g/100 g
INACTIVE INGREDIENTS: CARBOXYMETHYLCELLULOSE SODIUM; DIETHYL SEBACATE; POTASSIUM STEARATE; CETETH-20; SODIUM LAURYL SULFATE; GLYCERYL MONOSTEARATE; UREA; DIMETHICONE; ZINC OXIDE; WHITE WAX; STEARYL ALCOHOL; POLIDOCANOL; LIGHT MINERAL OIL; PROPYLENE GLYCOL; WATER; SILICON

Hi Vetic Ointment

Active ingredient Tolnaftate 1%

Purpose Antifungal

INDICATIONS AND USAGE

Uses ■for effective treatment of most athlete’s foot, jock itch, and ringworm
■prevents the recurrence of most athlete’s foot with daily use

Warnings
For external use only

Do not use ■ on children under 2 years of age unless directed by a doctor

When using this product ■ avoid contact with the eyes

Stop use and ask a doctor if
■ irritation occurs ■ there is no improvement within 4 weeks for athlete’s foot and ringworm, and within 2 weeks for jock itch

KEEP OUT OF REACH OF CHILDREN

Keep out reach of children. If swallowed, get medical help or contact a Poison Control Center right away.

Directions
■for the treatment of athlete’s foot, jock itch, and ringworm
■cleanse the affected area with soap and water and dry throughly
■apply a thin layer of the product over affected area twice daily (morning and night), or as directed by a doctor
■to prevent athlete’s foot
■cleanse the feet with soap and water and dry throughly
■apply a thin layer of the product to the feet once or twice daily (morning and/or night)
■supervise children in the use of this product
■for athlete’s foot
■pay special attention to spaces between the toes ■wear well-fitting, ventilated shoes ■change shoes and socks at least once daily
■for athlete’s foot and ringworm, use daily for 4 weeks. ■for jock itch, use daily for 2 weeks. ■if condition persists longer, consult a doctor ■this product is not effective on the scalp or nails

INACTIVE INGREDIENT

Inactive ingredients Carboxymethylcellulose sodium, diethyl sebacate, fragrance, glyceryl monostearate, lauromacrogol 400, light mineral oil, polyoxyethylene cetylether, potassium stearate, propylene glycol, simethicone, sodium lauryl sulfate, stearyl alcohol, urea, water, white wax, zinc oxide.

PACKAGE LABEL

hiveticointcart.jpg